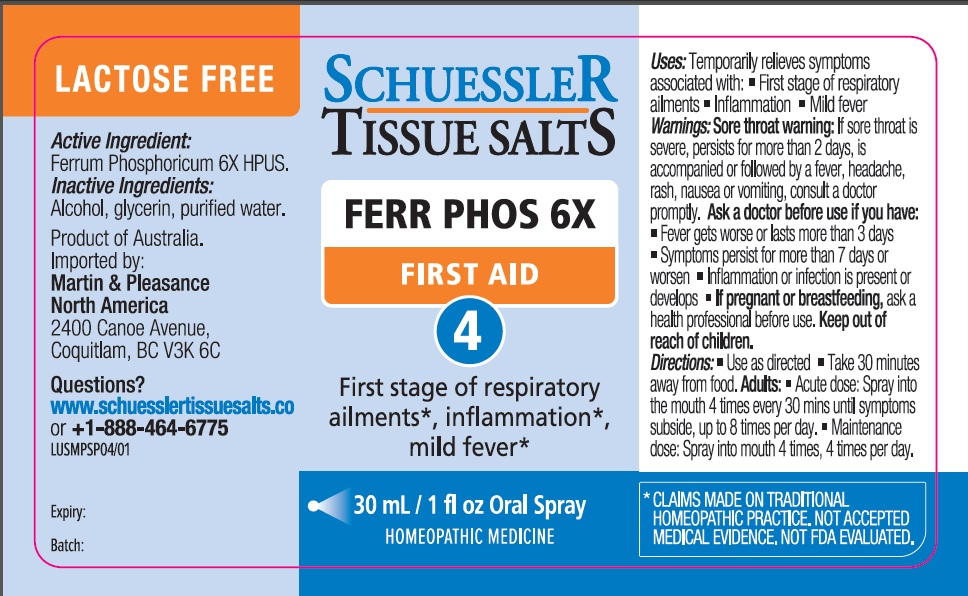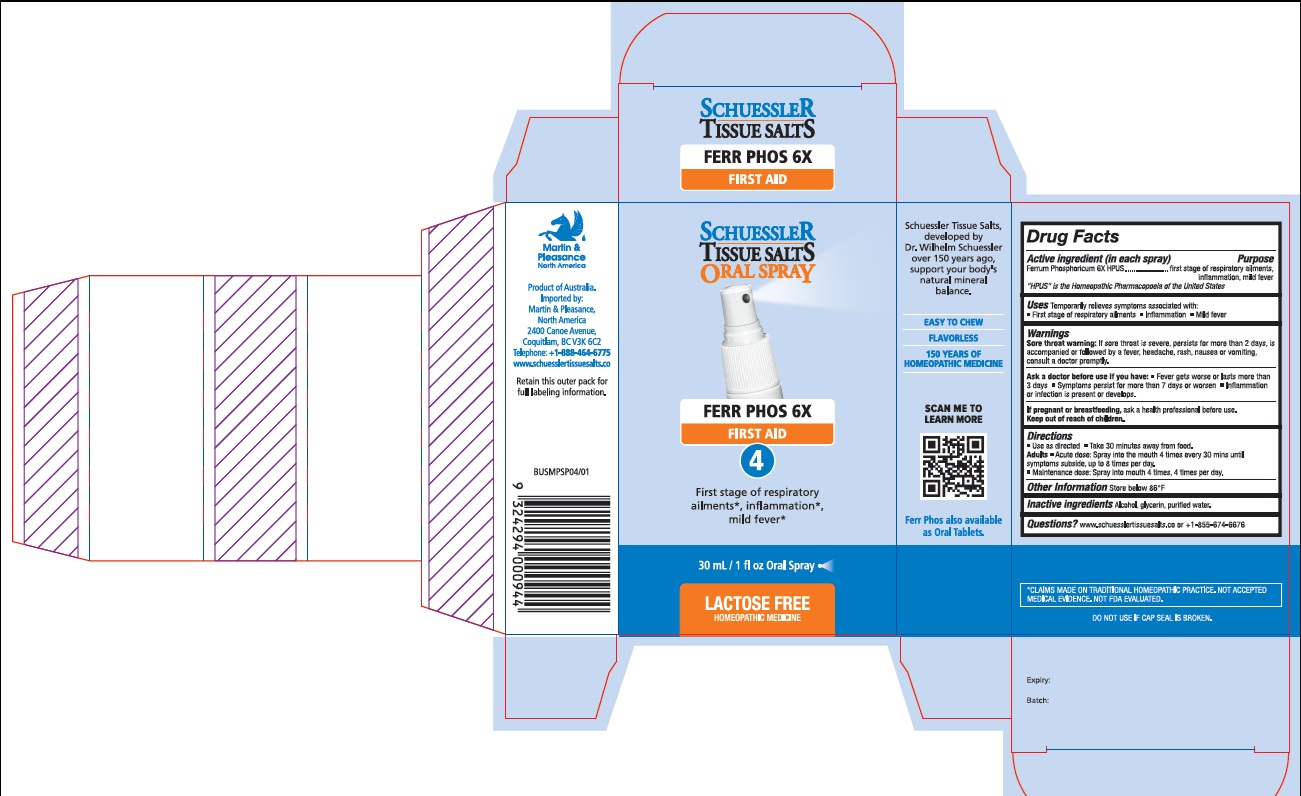 DRUG LABEL: Schuessler Tissue Salts Ferr Phos First Aid 4
NDC: 84999-004 | Form: SPRAY
Manufacturer: Martin & Pleasance Pty Ltd
Category: homeopathic | Type: HUMAN OTC DRUG LABEL
Date: 20250701

ACTIVE INGREDIENTS: FERROUS PHOSPHATE 6 [hp_X]/30 mL
INACTIVE INGREDIENTS: ALCOHOL; GLYCERIN; WATER

Active Ingredients (in each spray) Purpose

Ferrum Phosphoricum 6X HPUS first stage of respiratory ailments, inflammation, mild fever

" HPUS" is the Homeopathic Pharmacopoeia of the United States

Uses

- Temporarily relieves symptoms associated with:
- First stage of respiratory ailments
- Inflammation
- Mild fever

Warnings

Sore throat warning: If sore throat is severe, persists for more than 2 days, is accompanied or followed by a fever, headache, rash, nausea or vomiting, consult a doctor promptly.

Ask a doctor before use if you have:

- Fever gets worse or lasts more than 3 days
- Symptoms persist for more than 7 days or worsen
- Inflammation or infection is present or develops.

If pregnant or breastfeeding, ask a health professional before use. Keep out of reach of children.

Directions

- Use as directed
- Take 30 minutes away from food.

Adults

- Acute dose: Spray into the mouth 4 times every 30 mins until symptoms subside, up to 8 times per day.
- Maintenance dose: Spray into mouth 4 times, 4 times per day.

Other lnformation

Store below 86°F

Inactive Ingredients

Alcohol , Glycerin, water

Questions?www.schuesslertissuesalts.co or +I -855-67 4-6676